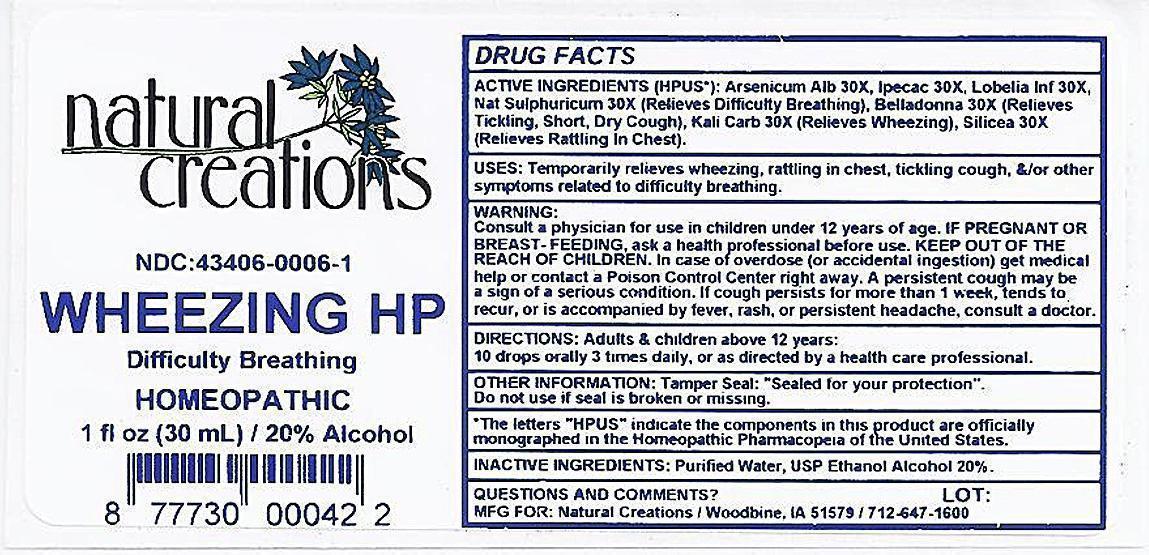 DRUG LABEL: Wheezing HP
NDC: 43406-0006 | Form: LIQUID
Manufacturer: Natural Creations, Inc.
Category: homeopathic | Type: HUMAN OTC DRUG LABEL
Date: 20121002

ACTIVE INGREDIENTS: ARSENIC TRIOXIDE 30 [hp_X]/1 mL; BELLADONNA LEAF 30 [hp_X]/1 mL; IPECAC 30 [hp_X]/1 mL; POTASSIUM CARBONATE 30 [hp_X]/1 mL; LOBELIA INFLATA 30 [hp_X]/1 mL; SODIUM SULFATE 30 [hp_X]/1 mL; SILICON DIOXIDE 30 [hp_X]/1 mL
INACTIVE INGREDIENTS: WATER; ALCOHOL

Wheezing HP

ACTIVE INGREDIENT

Active Ingredients (HPUS*): Arsenicum Album 30X, Belladonna 30X, Ipecacuanha 30X, Kali Carbonicum 30X, Lobelia Inflata 30X, Natrum Sulphuricum 30X, Silicea 30X

PURPOSE

Arsenicum Album 30X................................................Relieves Difficutly Breathing

Belladonna 30X.........................................................Relieves Tickling, Short, Dry Cough

Ipecacuanha 30X......................................................Relieves Difficulty Breathing

Kali Carbonicaum 30X...............................................Relieves Wheezzing

Lobelia 30X...............................................................Relieves Difficulty Breathing

INDICATIONS AND USAGE

USES Temprarily relieves wheezing, rattling in chest, tickling cough, &/or other symptoms related to difficulty breathing.

WARNING:

Consult a physician for use in children under 12 years of age. IF PREGNANT OR BREAST-FEEDING, ask a health care professional before use. KEEP OUT OF THE REACH OF CHILDREN. In case of overdose (or accidental ingestion) get medical help or contact a Poison Control Center right away. A persisten cough my be a sign of a serious condition. If cough persists for more than 1 week, tends to recur, or is accompanied by fever, rash, or persisten headache, consult a doctor.

DOSAGE AND ADMINISTRATION

DIRECTIONS: Adults and children above 12 years: 10 drops orally 3 times daily, or as directed by a health care professional.

OTHER INFORMATION: Tamper Seal: "Sealed for your protection."

Do not use if seal is broken or missing.

REFERENCES

*The letters "HPUS" indicate the components in the product are officially monographed in the Homeopathic Pharmacopeia of the United States.

INACTIVE INGREDIENTS: Purified Water, USP Ethanol Alcohol 20%

QUESTIONS AND COMMENTS?
MFG FOR: Natural Creations / Woodbine, IA / 51579 712.647.1600

LOT:

PURPOSE

USES: Temporarily relieves wheezing, rattling in chest, tickling cough, and/or other symptoms related to difficulty breathing.

KEEP OUT OF REACH OF CHILDREN

KEEP OUT OF THE REACH OF CHILDREN. In case of overdose (or accidental ingestion) get medical help or contact a Poison Control Center.

PACKAGE LABEL

NDC: 43406-0006-1

WHEEZING HP

Difficulty Breathing

HOMEOPATHIC

1 fl oz (30 mL) / 20% Alcohol

UPC: 877730000422